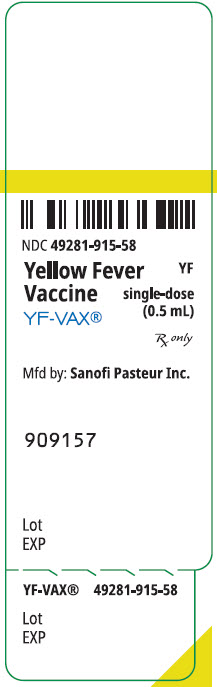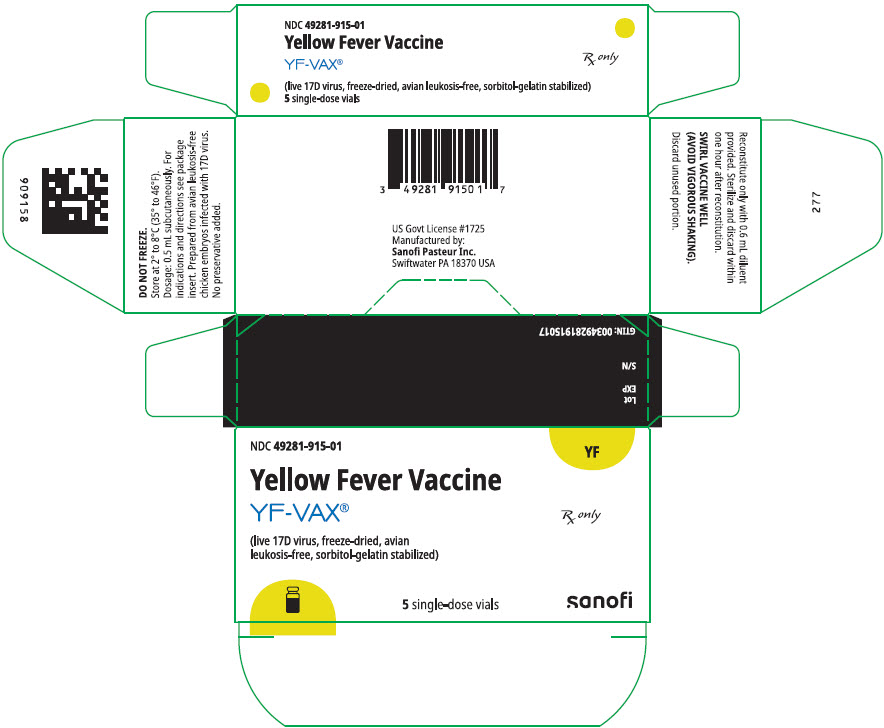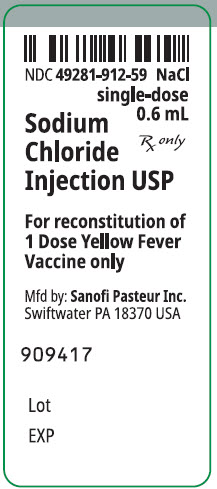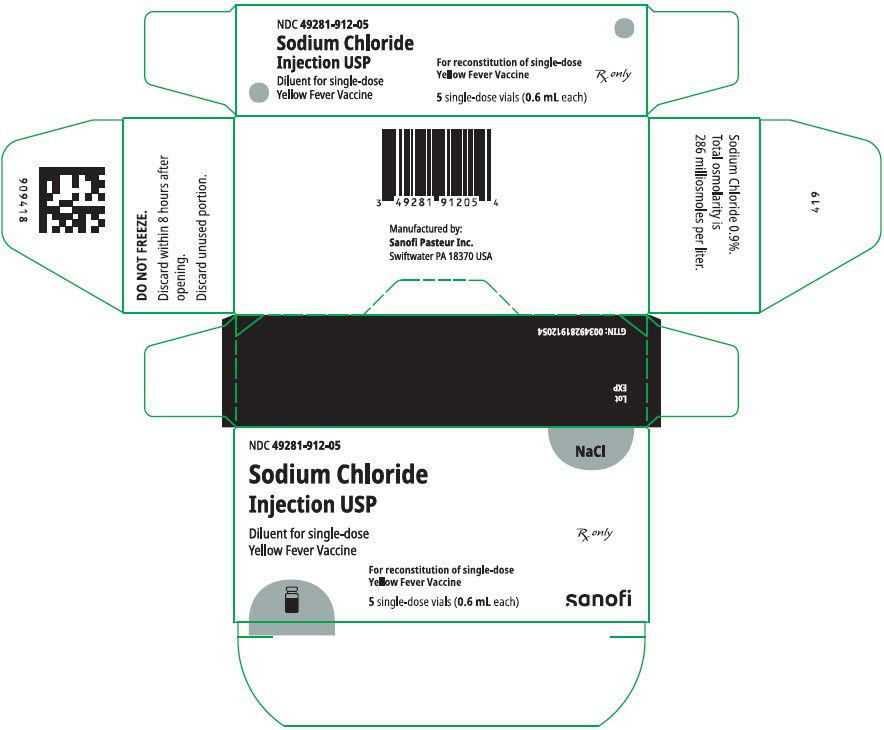 DRUG LABEL: YF-VAX
NDC: 49281-915 | Form: INJECTION, POWDER, LYOPHILIZED, FOR SUSPENSION
Manufacturer: Sanofi Pasteur Inc.
Category: other | Type: VACCINE LABEL
Date: 20250516

ACTIVE INGREDIENTS: YELLOW FEVER VIRUS STRAIN 17D-204 LIVE ANTIGEN 4.74 [PFU]/0.5 mL
INACTIVE INGREDIENTS: SORBITOL; GELATIN, UNSPECIFIED

YF-VAX®

AHFS Category: 80:12
Rx only

Yellow Fever Vaccine

DESCRIPTION

YF-VAX®, Yellow Fever Vaccine, for subcutaneous use, is prepared by culturing the 17D-204 strain of yellow fever virus in living avian leukosis virus-free (ALV-free) chicken embryos. The vaccine contains sorbitol and gelatin as a stabilizer, is lyophilized, and is hermetically sealed under nitrogen. No preservative is added. Each vial of vaccine is supplied with a separate vial of sterile diluent, which contains Sodium Chloride Injection USP – without a preservative. YF-VAX is formulated to contain not less than 4.74 log10 plaque forming units (PFU) per 0.5 mL dose throughout the life of the product. Before reconstitution, YF-VAX is a pinkish color. After reconstitution, YF-VAX is a slight pink-brown suspension.

The vial stoppers for YF-VAX and diluent are not made with natural rubber latex.

CLINICAL PHARMACOLOGY

Yellow fever is an acute viral illness caused by a mosquito-borne flavivirus. Most yellow fever virus infections are asymptomatic. In those individuals who develop disease, the clinical spectrum ranges from nonspecific flu-like illness with fever, malaise, prostration, headache, photophobia, generalized arthralgia and myalgia, nausea, and/or vomiting to potentially lethal pansystemic disease, most prominently involving the liver, kidneys, GI tract, and brain, with recrudescing fever, jaundice, renal failure, severe hemorrhage due to thrombocytopenia, and shock. (1) The case-fatality rate of yellow fever varies widely in different studies but is typically 20% or higher. Jaundice or other gross evidence of severe liver disease is associated with higher mortality rates.

Two live, attenuated yellow fever vaccines, strains 17D-204 and 17DD, were derived in parallel in the 1930s. Historical data suggest that these "17D vaccines" have identical safety and immunogenicity profiles. Vaccination with 17D strain vaccines is predicted to elicit an immune response identical in quality to that induced by wild-type infection. This response is presumed to result from initial infection of cells in the dermis or other subcutaneous tissues near the injection site, with subsequent replication and limited spread of virus leading to the processing and presentation of viral antigens to the immune system, as would occur during infection with wild-type yellow fever virus. The humoral immune response to the viral structural proteins, as opposed to a cell-mediated response, is most important in the protective effect induced by 17D vaccines. Yellow fever antibodies with specificities that prevent or abort infection of cells are detected as neutralizing antibodies in assays that measure the ability of serum to reduce plaque formation in tissue culture cells. The titer of virus neutralizing antibodies in sera of vaccinees is a surrogate for efficacy. A log10 neutralization index (LNI, measured by a plaque reduction assay) of 0.7 or greater was shown to protect 90% of monkeys from lethal intracerebral challenge. (2) This is the definition of seroconversion adopted for clinical trials of yellow fever vaccine. The standard has also been adopted by the World Health Organization (WHO) for efficacy of yellow fever vaccines in humans. (3)

In 24 uncontrolled studies conducted world-wide between 1962 and 1997 evaluating neutralizing antibody responses to 17D vaccines among a total of 2,529 adults and 991 infants and children, the seroconversion rate was greater than 91% in all but two studies and never lower than 81%. There were no significant age-related differences in immunogenicity. (1)

Five of these 24 studies were conducted in the US between 1962 and 1993 and included 208 adults who received YF-VAX. The seroconversion rate was 81% in one study involving 32 subjects and 97% to 100% in the other four studies. (1) (4) (5) (6) (7)

In 2001, YF-VAX was used as a control in a double-blind, randomized comparison trial with another 17D-204 vaccine, conducted at nine centers in the US. YF-VAX was administered to 725 adults ≥18 years old with a mean age of 38 years. Three hundred twelve of these subjects who received YF-VAX were evaluated serologically, and 99.3% of them seroconverted with a mean LNI of 2.21. The LNI was slightly higher among males compared to females and slightly lower among Hispanic and African-American subjects compared to others, but these differences were not associated with differences in protective effect of the vaccine. There was no difference in mean LNI for subjects <40 years old compared to subjects ≥40 years old. Due to the small number of subjects (1.7%) with prior flavivirus immunity, it was not possible to draw conclusions about the role of this factor in the immune response. (8)

For most healthy individuals, a single dose of yellow fever vaccine provides long-lasting protection. (9) (10) In controlled studies where the immune response to vaccination was evaluated, the small percentage of immunologically normal individuals who failed to develop an immune response to an initial vaccination typically did so upon re-vaccination. (11)

In two separate clinical trials of 17D-204 vaccines, 90% of subjects seroconverted within 10 days after vaccination, (12) and 100% of subjects seroconverted within 14 days. (1) Thus, International Health regulations stipulate that the vaccination certificate for yellow fever is valid 10 days after administration of YF-VAX. (13)

INDICATIONS AND USAGE

YF-VAX is indicated for active immunization for the prevention of yellow fever in persons 9 months of age and older in the following categories:

Persons Living in or Traveling to Endemic Areas

While the actual risk for contracting yellow fever during travel is probably low, variability of itineraries, behaviors and seasonal incidence of disease make it difficult to predict the actual risk for a given individual living in or traveling to a known endemic or epidemic area. Greater risk is associated with living in or traveling to areas of South America and Africa where yellow fever infection is officially reported at the time of travel and with traveling outside the urban areas of countries that do not officially report the disease but that lie in a yellow fever endemic zone.

Persons Traveling Internationally Through Countries with Yellow Fever

Some countries require an individual to have a valid International Certificate of Vaccination or Prophylaxis (ICVP) if the individual has been in countries either known or thought to harbor yellow fever virus. The certificate becomes valid 10 days after vaccination with YF-VAX. (13) (14)

Laboratory Personnel

Laboratory personnel who handle virulent yellow fever virus or concentrated preparations of the yellow fever vaccine virus strains may be at risk of exposure by direct or indirect contact or by aerosols. (14)

CONTRAINDICATIONS

Hypersensitivity

YF-VAX is contraindicated in anyone with a history of acute hypersensitivity reaction to any component of the vaccine. (See DESCRIPTION section.) Because the yellow fever virus used in the production of this vaccine is propagated in chicken embryos, do not administer YF-VAX to anyone with a history of acute hypersensitivity to eggs or egg products due to a risk of anaphylaxis. Less severe or localized manifestations of allergy to eggs or to feathers are not contraindications to vaccine administration and do not usually warrant vaccine skin testing. (See PRECAUTIONS section, Testing for Hypersensitivity Reactions subsection.) Generally, persons who are able to eat eggs or egg products may receive the vaccine. (14) (15)

Individuals Less Than 9 Months of Age

Vaccination with YF-VAX is contraindicated in infants less than 9 months of age due to an increased risk of encephalitis.

Vaccination with YF-VAX is also contraindicated in lactating women who are providing breastmilk to infants less than 9 months of age due to the potential for transmission of vaccine virus in breastmilk. (See PRECAUTIONS section, Nursing Mothers subsection.)

Immunosuppressed Individuals

Vaccination with YF-VAX, a live virus vaccine, is contraindicated in individuals with severe immunosuppression, including for example, those with acquired immunodeficiency syndrome, leukemia, lymphoma, thymic disease, generalized malignancy, and patients who are undergoing drug therapy (e.g., systemic corticosteroids, alkylating drugs, antimetabolites or other immunomodulatory drugs) or radiation therapy. Thymic disorders associated with abnormal immune cell function (e.g., myasthenia gravis, thymoma) may be an independent risk factor for the development of yellow fever vaccine-associated viscerotropic disease. (See WARNINGS section.) (16)

Do not administer YF-VAX to individuals with severe immunosuppression.

Family members of immunosuppressed persons, who themselves have no contraindications, may receive YF-VAX. (14) (17)

WARNINGS

Severe allergic reactions (e.g., anaphylaxis) may occur following the use of YF-VAX, even in individuals with no prior history of hypersensitivity to the vaccine components. Appropriate medical treatment and supervision must be available to manage possible anaphylactic reactions following administration of the vaccine.

Yellow fever vaccine-associated viscerotropic disease

Age greater than 60 years is a risk factor for yellow fever vaccine-associated viscerotropic disease (YEL-AVD) (14) which may present as non-specific multi-organ system failure or can be similar to fulminant yellow fever caused by wild-type yellow fever virus, with liver failure and internal bleeding, leading to death. (See ADVERSE REACTIONS section.) Available evidence suggests that the occurrence of this syndrome may depend upon undefined host factors, rather than intrinsic virulence of the yellow fever strain 17D vaccine, based on characterization of vaccine viruses isolated from individuals with YEL-AVD. YEL-AVD has been reported to occur only after the first dose of yellow fever vaccine; there have been no reports of YEL-AVD following booster dose. (17) The decision to vaccinate individuals 60 years of age and older needs to weigh the risks and benefits of vaccination and the risk for exposure to yellow fever virus. (18) (19) (20) (21)

Yellow fever vaccine-associated neurotropic disease

Age greater than 60 years and immunosuppression are risk factors for post-vaccinal encephalitis, also known as yellow fever vaccine-associated neurotropic disease (YEL-AND). (See ADVERSE REACTIONS section.) Almost all cases of YEL-AND have been in first-time vaccine recipients. (17) The decision to vaccinate individuals 60 years of age and older and immunosuppressed individuals needs to weigh the risks and benefits of vaccination and the risk for exposure to yellow fever virus.

PRECAUTIONS

General

Vaccination with YF-VAX may not protect 100% of individuals.

Do not administer YF-VAX by intravascular, intramuscular, or intradermal routes.

Use a separate, sterile syringe and needle for each patient to prevent transmission of blood borne infectious agents. Do not recap needles. Dispose of needles and syringes according to biohazard waste guidelines.

Testing for Hypersensitivity Reactions

Do not administer YF-VAX to an individual with a history of hypersensitivity to egg or chicken protein. (See CONTRAINDICATIONS section.) However, if an individual is suspected of being an egg-sensitive individual, the following test can be performed before the vaccine is administered:

1. Scratch, prick, or puncture test

Place a drop of a 1:10 dilution of the vaccine in physiologic saline on a superficial scratch, prick, or puncture on the volar surface of the forearm. Positive (histamine) and negative (physiologic saline) controls should also be used. The test is read after 15 to 20 minutes. A positive test is a wheal (superficial bump) 3 mm larger than that of the saline control, usually with surrounding erythema. The histamine control must be positive for valid interpretation. If the result of this test is negative, an intradermal (ID) test should be performed.

2. Intradermal test

Inject a dose of 0.02 mL of a 1:100 dilution of the vaccine in physiologic saline. Positive and negative control skin tests should be performed concurrently. A wheal 5 mm or larger than the negative control with surrounding erythema is considered a positive reaction.

If vaccination is considered essential despite a positive skin test, consider desensitization. (See DOSAGE AND ADMINISTRATION section, Desensitization subsection.)

Syncope

Syncope can occur following or even before vaccination. Procedures should be in place to prevent falling and injury and to manage syncope.

Information for Patients

Prior to administration of YF-VAX, ask potential vaccinees or their parents or guardians about their recent health status and history of yellow fever vaccination. Inform potential vaccinees or their parents or guardians about the benefits and risks of immunization and potential for adverse reactions to YF-VAX administration. Instruct vaccinees or their parents or guardians to report to their health-care providers all serious adverse events that occur up to 30 days post-vaccination.

All travelers should seek information regarding vaccination requirements by consulting with their health care providers. Such requirements may be strictly enforced for entry into certain countries, particularly for persons traveling from Africa or South America to Asia. Additional information is available from local health departments, the Centers for Disease Control and Prevention (CDC), and WHO. Travel agencies, international airlines, and/or shipping lines may also have up-to-date information. The vaccination center should complete, sign, and stamp an International Certificate of Vaccination and provide the certificate to the vaccinee. The immunization record should contain the date, lot number and manufacturer of the vaccine administered. Inform vaccinees that vaccination certificates are valid commencing 10 days after vaccination. (14)

Drug Interactions

Data are limited in regard to the interaction of YF-VAX with other vaccines.

- Measles (Schwartz strain) vaccine, diphtheria and tetanus toxoids and whole cell pertussis vaccine (DTP), (22) Hepatitis A and Hepatitis B vaccines, (5) (14) (23) (24) meningococcal vaccine, Menomune®A/C/Y/W-135, and typhoid vaccine, Typhim Vi®, (5) (14) (23) have been administered with yellow fever vaccine at separate injection sites.
- The potential for interference between yellow fever vaccine and rabies or Japanese encephalitis vaccines has not been established. (14)
- In a prospective study, persons given 5 cc of commercially available immune globulin did not experience alterations in immunologic responses to the yellow fever vaccine. (14) (25) (26)
- Although chloroquine inhibits replication of yellow fever vaccine in vitro, it does not appear to adversely affect antibody responses to yellow fever vaccine among persons receiving chloroquine. (14) (27)

Patients on Corticosteroid Therapy

Oral Prednisone or other systemic corticosteroid therapy, depending on dose and duration of exposure, may have an immunosuppressive effect on recipients of yellow fever vaccine that potentially decreases immunogenicity and increases the risk of adverse events. Intra-articular, bursal, or tendon injections with corticosteroids should not constitute an increased hazard to recipients of yellow fever vaccine.

Patients with Asymptomatic Human Immunodeficiency Virus (HIV) Infection

The rate of seroconversion following YF-VAX is reduced in individuals with asymptomatic HIV infection and appears to depend on HIV viral load and CD4 + T-cell count. (14) Therefore, documentation of a protective antibody response is recommended before travel. (See CLINICAL PHARMACOLOGY section.) For discussion of this subject and for documentation of the immune response to vaccine where it is deemed essential, contact the CDC at 1-970-221-6400.

Carcinogenesis, Mutagenesis, Impairment of Fertility

YF-VAX has not been evaluated for its carcinogenic or mutagenic potential or its effect on fertility.

Pregnancy

Animal reproduction studies have not been conducted with YF-VAX. It is also not known whether YF-VAX can cause fetal harm when administered to a pregnant woman or can affect reproduction capacity. YF-VAX should be given to a pregnant woman only if clearly needed.

YF-VAX has not been evaluated in pregnant women. However, based on experience of other yellow fever vaccines, the following findings have been determined for safety and effectiveness. A case-control study of Brazilian women found no significant difference in the odds ratio of spontaneous abortion among vaccinated women compared to a similar unvaccinated group. (28) In a separate study in Trinidad, 100 to 200 pregnant females were immunized, no adverse events related to pregnancy were reported. In addition, 41 cord blood samples were obtained from infants born to mothers immunized during the first trimester. One of these infants tested positive for IgM antibodies in cord blood. The infant appeared normal at delivery, and no subsequent adverse sequelae of infection were reported. However, this result suggests that transplacental infection with 17D vaccine viruses can occur. (29) In another study involving 101 Nigerian women, the majority of whom (88%) were in the third trimester of pregnancy, none of the 40 infants who were delivered in a hospital tested positive for IgM antibodies as a criterion for transplacental infection with vaccine virus. However, the percentage of pregnant women who seroconverted was reduced compared to a non-pregnant control group (38.6% vs. 81.5%). (30)

For further discussion of vaccination with YF-VAX during pregnancy and for documentation of a protective immune response to vaccine where it is deemed essential, contact the CDC at 1-970-221-6400.

Nursing Mothers

Because of the potential for serious adverse reactions in nursing infants from YF-VAX, a decision should be made whether to discontinue nursing or not to administer the vaccine, taking into account the importance of the vaccine to the mother. As of July, 2015, three vaccine-associated neurotropic disease cases have been reported worldwide in exclusively breastfed infants whose mothers were vaccinated with yellow fever vaccines, including one case reported after vaccination with YF-VAX. All three infants were diagnosed with encephalitis and were less than one month of age at the time of exposure. (17) Because age less than 9 months is a risk factor for yellow fever vaccine-associated neurotropic disease, YF-VAX is contraindicated in lactating women who are providing breastmilk to infants younger than 9 months of age. (See CONTRAINDICATIONS section.) Discuss the risks and benefits of vaccination with lactating women who are providing breastmilk to infants 9 months of age and older. (14)

Pediatric Use

Vaccination of infants less than 9 months of age is contraindicated because of the risk of yellow fever vaccine-associated neurotropic disease. (See CONTRAINDICATIONS and ADVERSE REACTIONS sections.)

Geriatric Use

There is an increased risk of severe systemic adverse reactions to YF-VAX in individuals 60 years of age and older. Monitor elderly individuals for signs and symptoms of yellow fever vaccine-associated viscerotropic disease, which typically occurs within 10 days post-vaccination. (See WARNINGS and ADVERSE REACTIONS sections.) (16) (31)

ADVERSE REACTIONS

Data from Clinical Studies

Adverse reactions to YF-VAX include mild headaches, myalgia, low-grade fevers, or other minor symptoms for 5 to 10 days. Local reactions including edema, hypersensitivity, pain or mass at the injection site have also been reported following yellow fever vaccine administration. Immediate hypersensitivity reactions, characterized by rash, urticaria, and/or asthma, occur principally among persons with histories of allergy to eggs or other substances contained in the vaccine.

Because clinical trials are conducted under widely varying conditions, adverse reaction rates observed in the clinical trials of a vaccine cannot be directly compared to rates in the clinical trials of another vaccine and may not reflect the rates observed in practice.

No placebo-controlled trial has assessed the safety of YF-VAX. However, between 1953 and 1994, reactogenicity of 17D-204 vaccine was monitored in 10 uncontrolled clinical trials. The trials included a total of 3,933 adults and 264 infants greater than 4 months old residing in Europe or in yellow fever endemic areas. Self-limited and mild local reactions consisting of erythema and pain at the injection site and systemic reactions consisting of headache and/or fever occurred in a minority of subjects (typically less than 5%) 5 to 7 days after immunization. In one study involving 115 infants age 4 to 24 months the incidence of fever was as high as 21%. Also in this study, reactogenicity of the vaccine was markedly reduced among a subset of subjects who had serological evidence of previous exposure to yellow fever virus. Only two of the ten studies provided diary cards for daily reporting; this method resulted in a slightly higher incidence of local and systemic complaints. YF-VAX was used as a control in a double-blind, randomized comparative trial with another 17D-204 vaccine, conducted at nine centers in the US. YF-VAX was administered to 725 adults ≥18 years old with a mean age of 38 years. Safety data were collected by diary card for days 1 through 10 after vaccination and by interview on days 5, 11, and 31. Among subjects who received YF-VAX, there were no serious adverse events, and 71.9% experienced non-serious adverse events judged to have been related to vaccination. Most of these were injection site reactions of mild to moderate severity. Four such local reactions were considered severe. Rash occurred in 3.2%, including two subjects with urticaria. Systemic reactions (headache, myalgia, malaise, and asthenia) were usually mild and occurred in 10% to 30% of subjects during the first few days after vaccination. The incidence of non-serious adverse reactions, including headache, malaise, injection site edema, and pain, was significantly lower in subjects >60 years compared to younger subjects. Adverse events were less frequent in the 1.7% of vaccinated subjects who had pre-existing immunity to yellow fever virus, compared to those without pre-existing immunity. (8)

Data from Post-marketing Experience

The following additional adverse events have been spontaneously reported during the post-marketing use of YF-VAX worldwide. Because these events are reported voluntarily from a population of uncertain size, it is not possible to estimate their frequency reliably or establish a causal relationship to vaccine exposure. This list includes adverse events based on one or more of the following factors: severity, frequency of reporting, or strength of evidence for a causal relationship to YF-VAX.

• General disorders and administration site conditions

Injection-site blisters

• Immune System Disorders (14)

Immediate hypersensitivity reactions or anaphylaxis, characterized by rash and/or urticaria and/or respiratory symptoms (e.g., dyspnea, bronchospasm, or pharyngeal edema) occur principally among persons with histories of allergies to egg or other substances contained in the vaccine.

• Nervous System Disorders (1) (32) (33) (34)

Isolated cases of Yellow Fever Vaccine-Associated Neurotropic Disease (YEL-AND), sometimes fatal, have been reported to occur within 30 days following vaccination with YF-VAX, and other yellow fever vaccines. (See WARNINGS section, Yellow fever vaccine-associated neurotropic disease subsection.) Age less than 9 months and congenital or acquired immunodeficiency have been identified as risk factors for this event. (See WARNINGS and CONTRAINDICATIONS sections.) Twenty-one cases of YEL-AND associated with all licensed 17D vaccines have been reported between 1952 and 2004. Eighteen of these cases were in children or adolescents. Fifteen of these cases occurred prior to 1960, thirteen of which occurred in infants 4 months of age or younger, and two of which occurred in infants six and seven months old. The incidence of vaccine-associated neurologic disease in infants less than 4 months old is estimated to be between 50 and 400 cases per 1,000,000, based on two historical reports where denominators are available. (33) (34) (35) A study in Senegal (34) described two fatal cases of encephalitis possibly associated with 17D-204 vaccination among 67,325 children between the ages of 6 months and 2 years, for an incidence rate of 3 per 100,000. The incidence of YEL-AND in the United States is less than 1:100,000 doses administered. (17)

Other neurological complications have included Guillain-Barré syndrome (GBS), acute disseminated encephalomyelitis (ADEM), and bulbar palsy.

• Infections and infestations

Isolated cases of Yellow Fever Vaccine-Associated Viscerotropic Disease YEL-AVD, formerly described as "Febrile Multiple Organ-System-Failure", sometimes fatal, have been reported following YF-VAX and other yellow fever vaccines. (See WARNINGS section, Yellow fever vaccine-associated viscerotropic disease subsection.) In the majority of cases reported, the onset of signs and symptoms was within 10 days after the vaccination. Initial signs and symptoms are non-specific and may include pyrexia, myalgia, fatigue and headache, potentially progressing quickly to liver and muscle cytolysis and possibly to thrombocytopenia, lymphopenia and acute renal failure. (18) The pathophysiological mechanism of such reactions has not been established. In some individuals with YEL-AVD a medical history of thymic disease has been reported. (36) Age older than 60 has also been identified as a risk factor for this event. (9) During surveillance in the U.S. between 1996 and 1998, four individuals (ages 63, 67, 76, and 79) became severely ill 2 to 5 days after vaccination with YF-VAX vaccine. Three of these 4 subjects died. The incidence rate for these serious adverse events was estimated at 1 per 400,000 doses of YF-VAX vaccine, based on the total number of doses administered in the U.S. civilian population during the surveillance period. (21) YEL-AVD has occurred after yellow fever vaccination in fewer than 1:100,000 U.S. vaccinees, (14) most commonly in individuals 60 years of age and older.

In a CDC analysis of data submitted to the Vaccine Adverse Events Reporting System (VAERS) between 1990 and 1998, the rate of systemic adverse events following vaccination was 2.5-fold higher in the 65 years or older age group (6.2 events per 100,000 doses of vaccine) compared to the 25 to 44 year-old age group (2.5 events per 100,000 doses of vaccine). (31)

Reporting of Adverse Events

To report SUSPECTED ADVERSE REACTIONS, contact the Pharmacovigilance Department, Sanofi Pasteur Inc., Discovery Drive, Swiftwater, PA 18370 at 1-800-822-2463 (1-800-VACCINE) or VAERS at 1-800-822-7967 or https://vaers.hhs.gov.

DOSAGE AND ADMINISTRATION

Primary Vaccination

Administer a single subcutaneous injection of 0.5 mL of reconstituted vaccine.

Additional Dosing Information

A single dose of yellow fever vaccine provides long-lasting protection to most healthy individuals. (See CLINICAL PHARMACOLOGY section.) However, an additional dose of yellow fever vaccine may be given to individuals who might not have had an adequate or sustained immune response to prior yellow fever vaccination and who continue to be at risk for exposure to yellow fever virus. Such individuals include women who were vaccinated during pregnancy, hematopoietic stem cell transplant recipients, and HIV-infected persons.

Booster Vaccination

A booster dose may be given to individuals who were last vaccinated against yellow fever at least 10 years prior and who are at increased risk for yellow fever disease either because of location and duration of travel or because of more consistent exposure to virulent virus. Such individuals include travelers who plan to spend a prolonged period in endemic areas or who plan to travel to highly endemic areas such as rural West Africa, and laboratory personnel who handle virulent yellow fever virus or concentrated preparations of the yellow fever vaccine virus strains. (10)

Some countries may require for entry evidence of a valid yellow fever vaccination (i.e., ICVP) within the previous 10 years for certain individuals, depending on prior travel itinerary. A booster dose of YF-VAX may be given to satisfy this requirement. (10) (37)

Concomitant Administration with other Vaccines

Limited data are available related to administration of YF-VAX with other vaccines and the potential for immune interference. (See PRECAUTIONS section, Drug Interactions subsection.) In instances where vaccines are given concomitantly, administer injections using separate syringes at separate sites. Do not combine or mix YF-VAX with any other vaccine. When not administered concomitantly, wait at least 4 weeks between administration of YF-VAX and other live vaccines. (14)

Vaccine Preparation

YF-VAX is supplied as two separate vials: a lyophilized powder (Vial 1) to be reconstituted with the diluent, Sodium Chloride Injection USP (Vial 2). A single dose, after reconstitution, is 0.5 mL.

- Reconstitute the vaccine using only the diluent supplied (0.6 mL single dose vial of Sodium Chloride Injection USP for single dose vial of vaccine). After removing the "flip-off" caps, cleanse the vaccine and diluent vial stoppers with a suitable germicide. Do not remove the vial stoppers or metal seals holding them in place. Using aseptic technique, use a suitable sterile needle and syringe to withdraw the volume of supplied diluent shown on the diluent label and slowly inject the diluent into the vial containing the vaccine. Allow the reconstituted vaccine to sit for one to two minutes and then carefully swirl mixture until a uniform suspension is achieved. Avoid vigorous shaking as this tends to cause foaming of the suspension. Do not dilute reconstituted vaccine. Use aseptic technique and a separate sterile needle and syringe to withdraw each 0.5 mL dose from the single dose vial of reconstituted vaccine.
- Before reconstitution, YF-VAX is a pinkish color. After reconstitution, YF-VAX is a slight pink-brown suspension. Parenteral drug products should be inspected visually for particulate matter and discoloration prior to administration, whenever solution and container permit. If either of these conditions exists, do not administer the vaccine.
- Administer the single dose of 0.5 mL subcutaneously using a suitable sterile needle.
- Use YF-VAX within 60 minutes of reconstituting the single dose vial.
- Discard unused portion.

Properly dispose of all reconstituted vaccine and containers that remain unused after one hour according to locally approved guidelines (e.g. sterilized or disposed in red hazardous waste containers). (14)

Desensitization

If immunization is imperative and the individual has a history of severe egg sensitivity and has a positive skin test to the vaccine, this desensitization procedure may be used to administer the vaccine. The following successive doses should be administered subcutaneously at 15 to 20 minute intervals:

1. 0.05 mL of 1:10 dilution
2. 0.05 mL of full strength
3. 0.10 mL of full strength
4. 0.15 mL of full strength
5. 0.20 mL of full strength

Desensitization should only be performed under the direct supervision of a physician experienced in the management of anaphylaxis with necessary emergency equipment immediately available.

HOW SUPPLIED

YF-VAX is supplied as a two-vial presentation in separate cartons as follows:

Carton | Carton NDC Number | Vial NDC Number
Carton of 5 single-dose vials of Yellow Fever Vaccine YF-VAX (lyophilized powder; Vial 1) | 49281-915-01 | 49281-915-58
Carton of 5 single-dose vials of Sodium Chloride Injection USP (diluent; Vial 2) | 49281-912-05 | 49281-912-59

The vial stoppers for YF-VAX vaccine and diluent are not made with natural rubber latex.

YF-VAX (Yellow Fever Vaccine) in the US is supplied only to designated Yellow Fever Vaccination Centers authorized to issue certificates of Yellow Fever Vaccination. Location of the nearest Yellow Fever Vaccination Centers may be obtained from the Centers for Disease Control and Prevention, Atlanta, GA 30333, state or local health departments.

STORAGE

Store at 2° to 8°C (35° to 46°F). DO NOT FREEZE.

Do not use vaccine after expiration date. YF-VAX does not contain a preservative.

The following stability information for YF-VAX is provided for those countries or areas of the world where an adequate cold chain is a problem and inadvertent exposure to abnormal temperatures has occurred. Half-life is reduced from approximately 14 days at 35° to 37°C to 3-4.5 days at 45° to 47°C.

REFERENCES

1 Monath TP et al. Yellow fever vaccine. In: Plotkin SA, Orenstein WA and Offit PA, eds. Vaccines. 6th Ed. Elsevier Saunders Inc. 2013:870-968.
2 Mason RA, et al. Yellow fever vaccine: Direct challenge of monkeys given graded doses of 17D vaccine. Appl Microbiol 1973;25(4):539-44.
3 Recommendations to assure the quality, safety and efficacy of live attenuated yellow fever vaccines. WHO Technical Report Series. 2013;978:264.
4 Wisseman CL, et al. Immunological studies with Group B arthropod-borne viruses. Am J Trop Med Hyg 1962;11:550-61.
5 Dukes C, et al. Safety and Immunogenicity of Simultaneous Administration of Typhim Vi (TV), YF-VAX (YV), and Menomune (MV). [abstract]. American Society for Microbiology. The 36th Interscience Conference on Antimicrobial Agents and Chemotherapy (ICAAC): 1996; September 15-18:159.
6 Meyer HM, et al. Response of Volta children to jet inoculation of combined live measles, smallpox, and yellow fever vaccines. Bull World Health Org 1964;30:783-94.
7 Jackson J, et al. Comparison of Antibody Response and Patient Tolerance of Yellow Fever Vaccine Administered by the Bioject Needle-Free Injection System versus Conventional Needle/Syringe Injection. Third International Conference on Travel Medicine; Paris 1993;April:25-29;264:209.
8 Monath TP, et al. Comparative safety and immunogenicity of two yellow fever 17D vaccines (ARILVAX and YF-VAX) in a Phase III multicenter, double-blind clinical trial. Am J Trop Med Hyg 66(5)2002;533-41.
9 World Health Organization (WHO). Yellow fever vaccine - position paper. Wkly Epid Rec 2003;40(78):349-60.
10 Staples JE et al. Yellow Fever Vaccine Booster Doses: Recommendations of the Advisory Committee on Immunization Practices, 2015. MMWR 2015;64(23):647-50.
11 Bonnevie-Nielson V, et al. Lymphocytic 2',5' - Oligoadenylate synthetase activity increases prior to the appearance of neutralizing antibodies and Immunoglobulin M and Immunoglobulin G antibodies after primary and secondary immunization with yellow fever vaccine. Clin Diag Lab Immunol 1995;2:302-6.
12 Smithburn KC, et al. Immunization against yellow fever: Studies on the time of development and the duration of induced immunity. Am J Trop Med Page 7 of 8 Hyg 1945;45:217-23.
13 World Health Organization (WHO). International Health Regulations (2005) (2nd edition). Geneva 2008:54-5.
14 Recommendations of the Advisory Committee on Immunization Practices (ACIP). Yellow Fever Vaccine. MMWR 2010;59(RR-7):1-32.
15 Centers for Disease Control and Prevention. General Recommendations on Immunization. Recommendations of the Advisory Committee on Immunization Practices (ACIP). MMWR 2011;60(No. RR2):(1-64).
16 Sanofi Pasteur Inc. Data on File – 080601;120104.
17 Centers for Disease Control and Prevention. CDC Health Information for International Travel 2016. New York: Oxford University Press 2016;3:346-60.
18 Martin M, et al. Fever and multisystem organ failure associated with 17D-204 yellow fever vaccination: a report of four cases. Lancet 2001;358:98-104.
19 Galler R, et al. Phenotypic and molecular analyses of yellow fever 17DD vaccine viruses associated with serious adverse events in Brazil. Virology 2001;290:309-19.
20 Chan RC, et al. Hepatitis and death following vaccination with yellow fever 17D-204 vaccine. Lancet 2001;358:121-2.
21 Vasconcelos PFC, et al. Serious adverse events associated with yellow fever 17DD vaccine in Brazil: a report of two cases. Lancet 2001;358:91-7.
22 Ruben FL, et al. Simultaneous administration of smallpox, measles, yellow fever, and diphtheria-pertussis-tetanus antigens to Nigerian children. Bull WHO 1973;48:175-81.
23 Dumas R, et al. Safety and immunogenicity of a new inactivated hepatitis A vaccine and concurrent administration with a typhoid fever vaccine or a typhoid fever + yellow fever vaccine. Adv Therapy 1997;14:160-7.
24 Coursaget P, et al. Simultaneous injection of plasma-derived or recombinant hepatitis B vaccines with yellow fever and killed polio vaccines. Vaccine 1995;13:109-11.
25 Kaplan JE, et al. The effect of immune globulin on the response to trivalent oral poliovirus and yellow fever vaccinations. Bull WHO 1984;62(4):585-90.
26 Edupuganti S, et al. A Randomized, Double-Blind, Controlled Trial of the 17D Yellow Fever Virus Vaccine Given in Combination with Immune Globulin or Placebo: Comparative Viremia and Immunogenicity. Am J Trop Med Hyg 2013;88(1):172-7.
27 Tsai TF, et al. Chloroquine does not adversely affect the antibody response to yellow fever vaccine. J Infect Dis 1986;154(4):726-7.
28 Nishioka SA, et al. Yellow fever vaccination during pregnancy and spontaneous abortion: a case-control study. Trop Med Int Health 1998;3(1):29-33.
29 Tsai TF, et al. Congenital yellow fever virus infection after immunization in pregnancy. J Infect Dis 1993;168:1520-1523.
30 Nasidi A, et al. Yellow fever vaccination and pregnancy: a four-year prospective study. Transactions of the Royal Society of Tropical Medicine and Hygiene 1993;87:337-9.
31 Martin M, et al. Advanced age a risk factor for illness temporally associated with yellow fever vaccination. Emerg Infect Dis 2001;7:945-51.
32 Jennings AD, et al. Analysis of a yellow fever virus isolated from a fatal case of vaccine-associated human encephalitis. J Infect Dis 1994;169:512-8.
33 Louis JJ, et al. A case of encephalitis after 17D strain yellow fever vaccination. Pediatr 1981;36(7):547-50.
34 Rey M, et al. Epidemiological and clinical aspects of encephalitis following yellow fever vaccination. Bull Soc Méd Afr Noire Lgue fr 1966;v XI,(3),560-74.
35 Stuart G. Reactions following vaccination against yellow fever. In Smithburn KC, Durieux C, Koerber R, et al (eds.). Yellow Fever Vaccination. Geneva, WHO 1956;143-189.
36 Data on file at sanofi pasteur. Global Pharmacovigilance Department Rationale for adding 'thymic disease' in the CCDS of AvP France Yellow Fever Vaccine Nov 2004.
37 World Health Organization (WHO). Vaccines and vaccination against yellow fever. WHO position paper - June 2013. Wkly Epid Rec 2013;27(88):269-84.

YF-VAX, Menomune, and Typhim Vi are registered trademarks of Sanofi Pasteur and its subsidiaries.

Product Information as of April 2025.

Manufactured by:

Sanofi Pasteur Inc.

Swiftwater, PA 18370 USA

PRINCIPAL DISPLAY PANEL - 0.5 mL Vial Label

NDC 49281-915-58
Yellow Fever
Vaccine
YF-VAX®

YF

single-dose
(0.5 mL)

Rx only

Mfd by: Sanofi Pasteur Inc.

909157

Lot
EXP

PRINCIPAL DISPLAY PANEL - 5 Vial Package - NDC 49281-915

NDC 49281-915-01

YF

Yellow Fever Vaccine
YF-VAX®

Rx only

(live 17D virus, freeze-dried, avian
leukosis-free, sorbitol-gelatin stabilized)

5 single-dose vials

sanofi

PRINCIPAL DISPLAY PANEL - 0.6 mL Vial Label

NDC 49281-912-59
NaCl
single-dose
0.6 mL

Sodium
Chloride
Injection USP

Rx only

For reconstitution of
1 Dose Yellow Fever
Vaccine only

Mfd by: Sanofi Pasteur Inc.
Swiftwater PA 18370 USA

909417

Lot
EXP

PRINCIPAL DISPLAY PANEL - 5 Vial Package - NDC 49281-912

NDC 49281-912-05
NaCl

Sodium Chloride
Injection USP

Diluent for single-dose
Yellow Fever Vaccine

Rx only

For reconstitution of single-dose
Yellow Fever Vaccine

5 single-dose vials (0.6 mL each)

sanofi